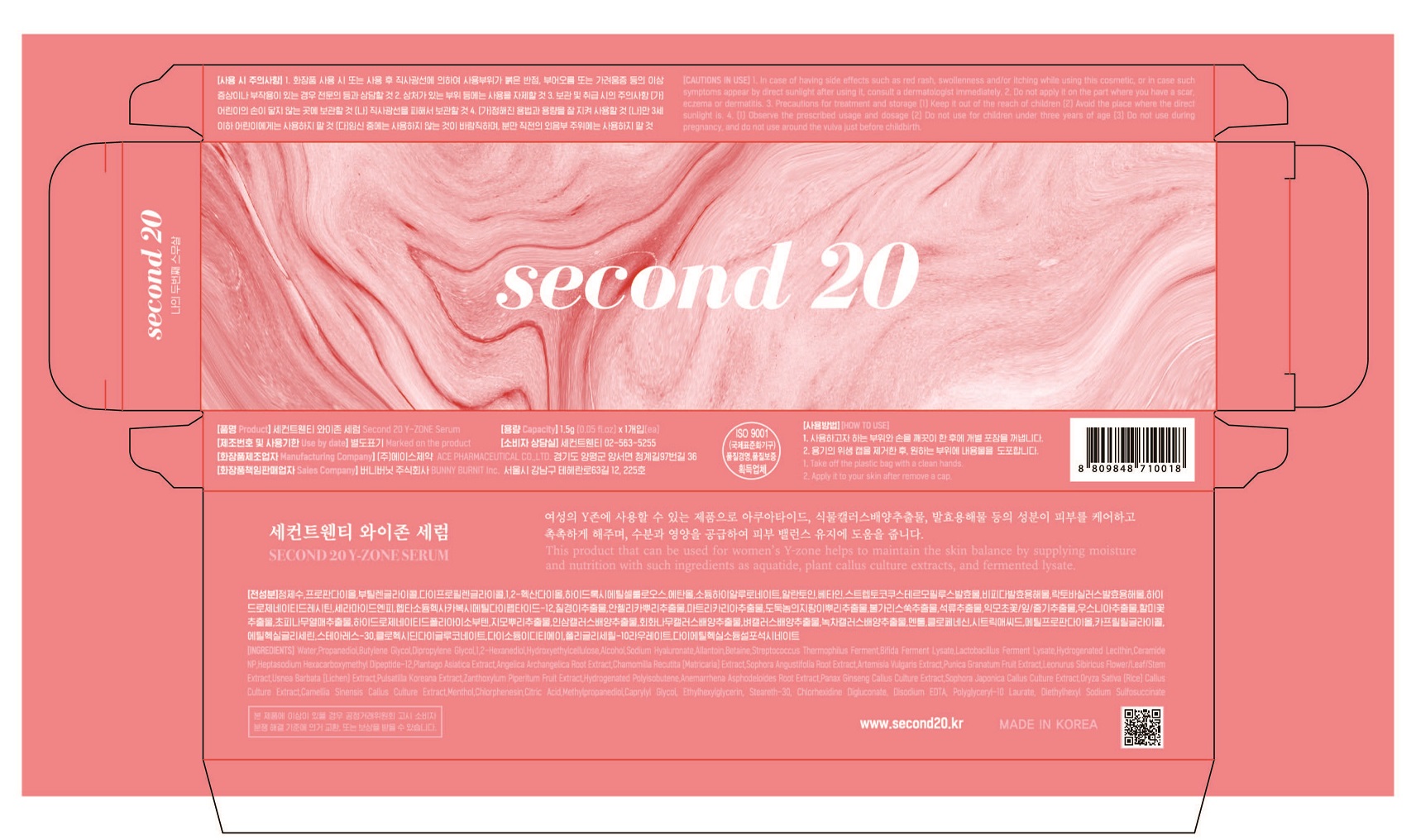 DRUG LABEL: Second 20 Y-ZONE Serum
NDC: 74196-0006 | Form: LIQUID
Manufacturer: ACE PHARMACEUTICAL CO LTD
Category: otc | Type: HUMAN OTC DRUG LABEL
Date: 20220113

ACTIVE INGREDIENTS: PROPANEDIOL 2 g/100 g
INACTIVE INGREDIENTS: WATER; ALLANTOIN

Drug Facts

ACTIVE INGREDIENT

PROPANEDIOL

INACTIVE INGREDIENT

Water
Butylene Glycol
Dipropylene Glycol
1,2-Hexanediol
Hydroxyethylcellulose
Alcohol
Sodium Hyaluronate
Allantoin
Betaine
Streptococcus Thermophilus Ferment
Bifida Ferment Lysate
Lactobacillus Ferment Lysate
Hydrogenated Lecithin
Ceramide NP
Heptasodium Hexacarboxymethyl Dipeptide-12
Plantago Asiatica Extract
Angelica Archangelica Root Extract
Chamomilla Recutita (Matricaria) Extract
Sophora Angustifolia Root Extract
Artemisia Vulgaris Extract
Punica Granatum Fruit Extract
Leonurus Sibiricus Flower/Leaf/Stem Extract
Usnea Barbata (Lichen) Extract
Pulsatilla Koreana Extract
Zanthoxylum Piperitum Fruit Extract
Hydrogenated Polyisobutene
Anemarrhena Asphodeloides Root Extract
Panax Ginseng Callus Culture Extract
Sophora Japonica Callus Culture Extract
Oryza Sativa (Rice) Callus Culture Extract
Camellia Sinensis Callus Culture Extract
Menthol
Chlorphenesin
Citric Acid
Methylpropanediol
Caprylyl Glycol
Ethylhexylglycerin
Steareth-30
Chlorhexidine Digluconate
Disodium EDTA
Polyglyceryl-10 Laurate
Diethylhexyl Sodium Sulfosuccinate

PURPOSE

1. Take off the plastic bag with a clean hands.
2. Apply it to your skin after remove a cap

KEEP OUT OF REACH OF THE CHILDREN

INDICATIONS AND USAGE

apply proper amount to the skin and gently massage

WARNINGS

1. In case of having side effects such as red rash, swollenness and/or itching while using this cosmetic, or in case such symptoms appear by direct sunlight after using it, consult a dermatologist immediately. 2. Do not apply it on the part where you have a scar, eczema or dermatitis. 3. Precautions for treatment and storage (1) Keep it out of the reach of children (2) Avoid the place where the direct sunlight is. 4. (1) Observe the prescribed usage and dosage (2) Do not use for children under three years of age (3) Do not use during pregnancy, and do not use around the vulva just before childbirth.

DOSAGE AND ADMINISTRATION

for external use only